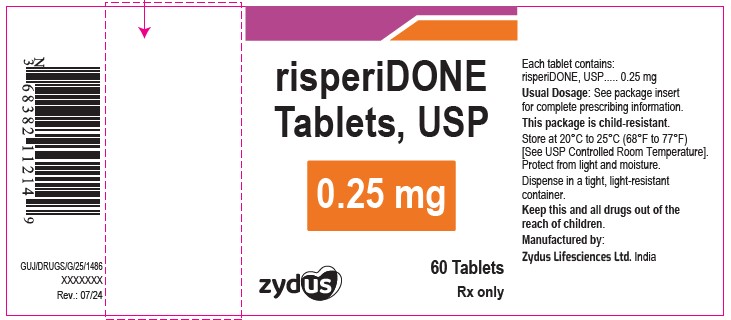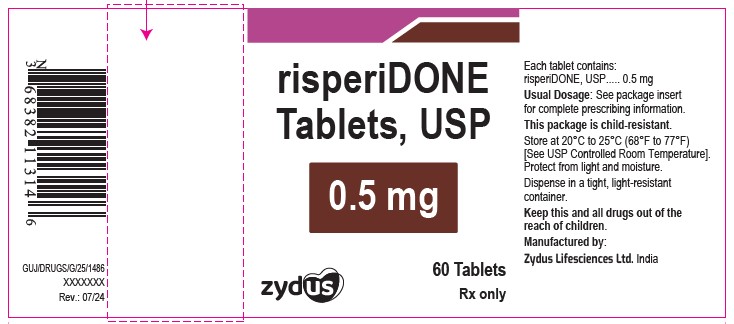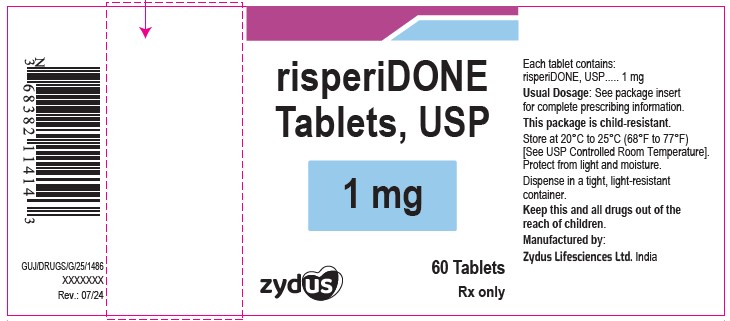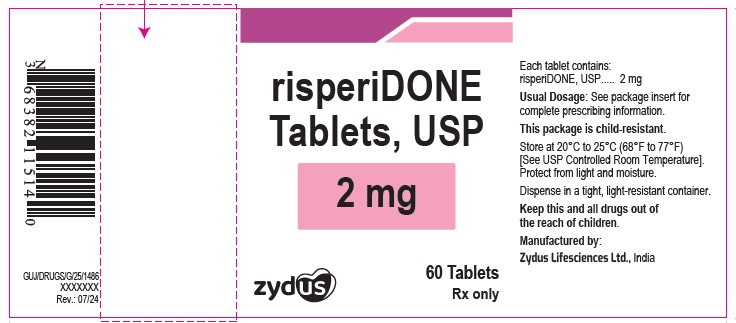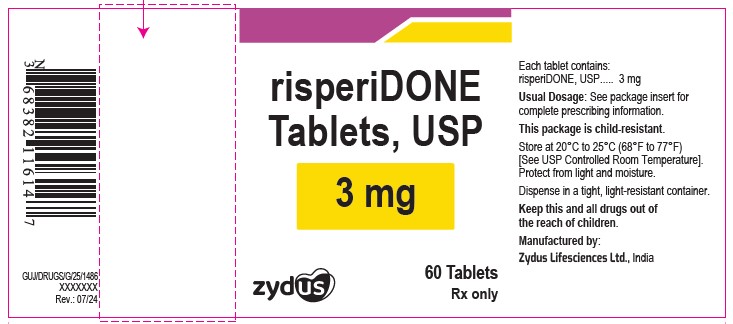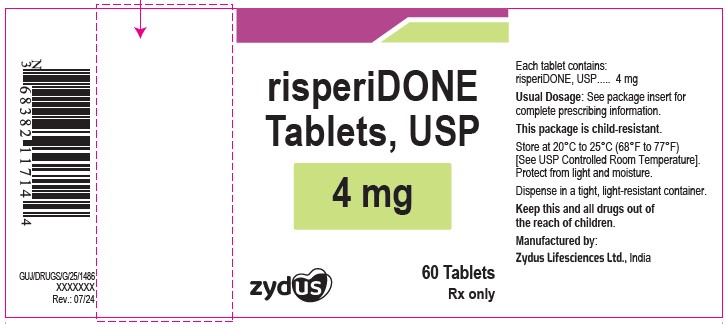 DRUG LABEL: risperidone
NDC: 65841-665 | Form: TABLET, FILM COATED
Manufacturer: Zydus Lifesciences Limited
Category: prescription | Type: HUMAN PRESCRIPTION DRUG LABEL
Date: 20240812

ACTIVE INGREDIENTS: RISPERIDONE 0.25 mg/1 1
INACTIVE INGREDIENTS: FERRIC OXIDE YELLOW; HYPROMELLOSES; LACTOSE MONOHYDRATE; MAGNESIUM STEARATE; PROPYLENE GLYCOL; SODIUM LAURYL SULFATE; TITANIUM DIOXIDE; FERRIC OXIDE RED; CELLULOSE, MICROCRYSTALLINE; STARCH, CORN

RISPERIDONE TABLETS

PACKAGE LABEL.PRINCIPAL DISPLAY PANEL

Risperidone Tablets USP, 0.25 mg

NDC 65841-665-14

60 tablets

Rx only

Risperidone Tablets USP, 0.5 mg

NDC 65841-666-14

60 tablets

Rx only

Risperidone Tablets USP, 1 mg

NDC 65841-667-14

60 Tablets

Rx only

Risperidone Tablets USP, 2 mg

NDC 65841-668-14

60 Tablets

Rx only

Risperidone Tablets USP, 3 mg

NDC 65841-669-14

60 Tablets

Rx only

Risperidone Tablets USP, 4 mg

NDC 65841-670-14

60 Tablets

Rx only